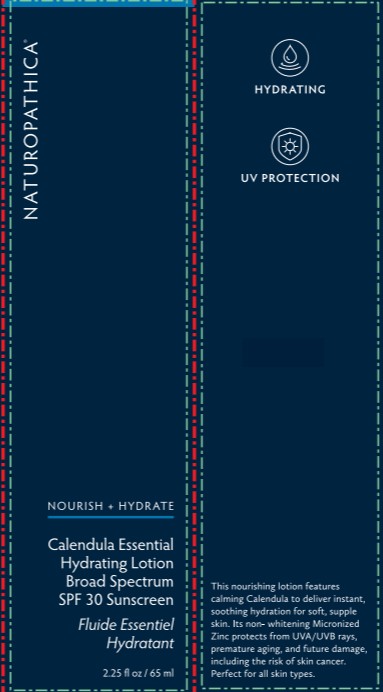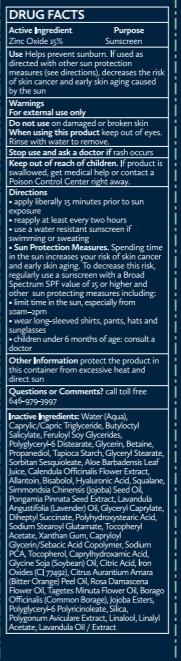 DRUG LABEL: Calendula Essential Hydrating Broad Spectrum SPF 30 Sunscreen
NDC: 64657-007 | Form: LOTION
Manufacturer: Naturopathica Holistic Health
Category: otc | Type: HUMAN OTC DRUG LABEL
Date: 20251023

ACTIVE INGREDIENTS: ZINC OXIDE 150 mg/1 mL
INACTIVE INGREDIENTS: CAPRYLIC/CAPRIC TRIGLYCERIDE; LAVANDULA ANGUSTIFOLIA (LAVENDER) OIL; HYDROLYZED JOJOBA ESTERS; POLYGONUM AVICULARE TOP; CAPRYLHYDROXAMIC ACID; BISABOLOL; GLYCERYL STEARATE; GLYCERYL CAPRATE; BORAGO OFFICINALIS WHOLE; LINALYL ACETATE; WATER; POLYHYDROXYSTEARIC ACID (2300 MW); POLYGLYCERYL-6 DISTEARATE; ALLANTOIN; CAPRYLOYL GLYCERIN/SEBACIC ACID COPOLYMER (2000 MPA.S); DIHEPTYL SUCCINATE; ROSA DAMASCENA FLOWER OIL; PROPANEDIOL; LINALOOL; SODIUM PCA; TOCOPHEROL; GLYCERIN; SORBITAN SESQUIOLEATE; SODIUM STEAROYL GLUTAMATE; POLYGLYCERYL-6 POLYRICINOLEATE; BUTYLOCTYL SALICYLATE; HYALURONIC ACID; SQUALANE; GLYCINE SOJA (SOYBEAN) OIL UNSAPONIFIABLES; PONGAMIA PINNATA SEED; CITRUS AURANTIUM AMARA (BITTER ORANGE) PEEL OIL; BETAINE; STARCH, TAPIOCA; ALOE BARBADENSIS LEAF JUICE; CALENDULA OFFICINALIS FLOWER; JOJOBA OIL; XANTHAN GUM; TAGETES MINUTA FLOWER OIL

Active Ingredients

Purpose

Zinc Oxide 15% ..............................................Sunscreen

Purpose

Zinc Oxide 15%..............................................Sunscreen

Uses

Helps prevent sunburn

if used as directed with other sun protection measures (see Directions), decreases the risk of skin cancer and early skin aging caused by the sun

WARNINGS

For external use only

Do not use on damaged or broken skin

WHEN USING

keep outof eyes.

Rinse with water to remove

Stop use and ask a doctor if rash occurs

Keep out of reach of children. If swallowed, get medical help or contact a Poison Control Center right away.

Directions

Apply liberally 15 minutes before sun exposure

Reapply at least every 2 hours

use a water resistant sunscreen if swimming or sweating

Sun Protection Measures. Spending time in the sun increases your risk of skin cancer and early skin aging. To decrease this risk, regularly use a sunscreen with a Broad Spectrum SPF value of 15 or higher and other sun protection measures including:

limit time in the sun, especially from 10 a.m.-2 p.m.

wear long-sleeved shirts, pants, hats and sunglasses

Children under 6 months of age: ask a doctor

OTHER SAFETY INFORMATION

Protect the product in this container from excessive heat and direct sun

QUESTIONS

Questions or Commets? call toll free 646-979-3997

INACTIVE INGREDIENT

Inactive Ingredients: Water (Aqua), Caprylic/Capric Triglyceride, Butyloctyl Salicylate, Feruloyl Soy Glycerides, Polyglyceryl-6 Distearate, Glycerin, Betaine, Propanediol, Tapioca Starch, Glyceryl Stearate, Sorbitan Sesquioleate, Aloe Barbadensis Leaf Juice, Calendula Officinalis Flower Extract, Allantoin, Bisabolol, Hyaluronic Acid, Squalane, Simmondsia Chinensis (Jojoba) Seed Oil, Pongamia Pinnata Seed Extract, Lavandula Angustifolia (Lavender) Oil, Glyceryl Caprylate, Dilheptyl Succinate, Polyhydroxystearic Acid, Sodium Stearoyl Glutamate, Tocopheryl Acetate, Xanthan Gum, Capryloyl Glycerin/Sebacic Acid Copolymer, Sodium PCA, Tocopherol, Caprylhydroxamic Acid, Glycine Soja (Soybean) Oil, Citric Acid, Iron Oxides (Cl 77492), Citrus Aurantium Amara (Bitter Orange) Peel Oil, Rosa Damascena Flower Oil, Tagetes Minuta Flower Oil, Borago Officinalis (Common Borage), Jojoba Esters, Polyglyceryl-6 Polyricinoleate, Silica, Polygonum Aviculare Extract, Linalool, Linalyl Acetate, Lavandula Oil / Extract